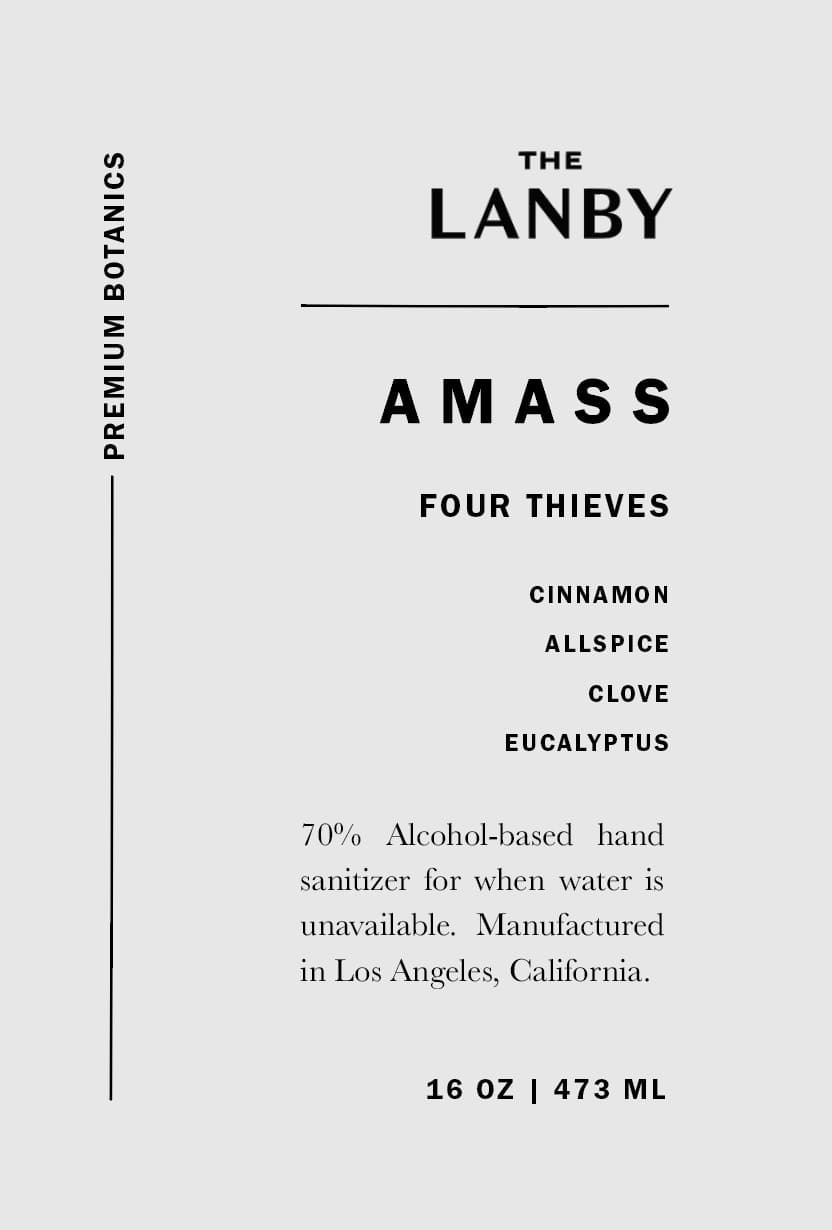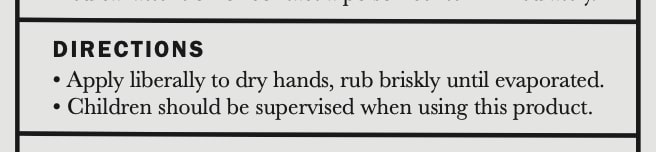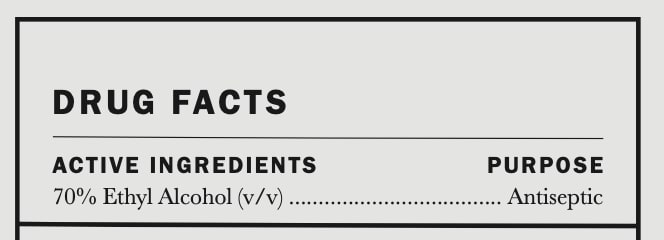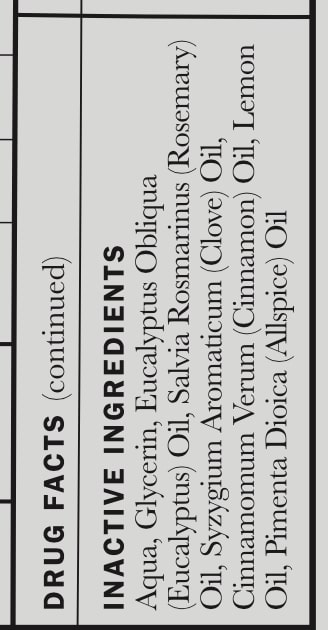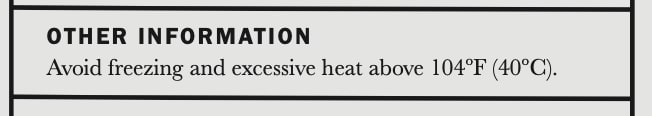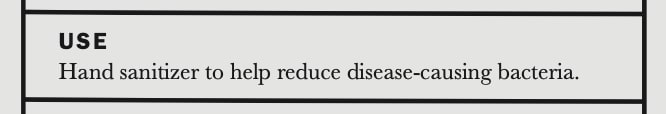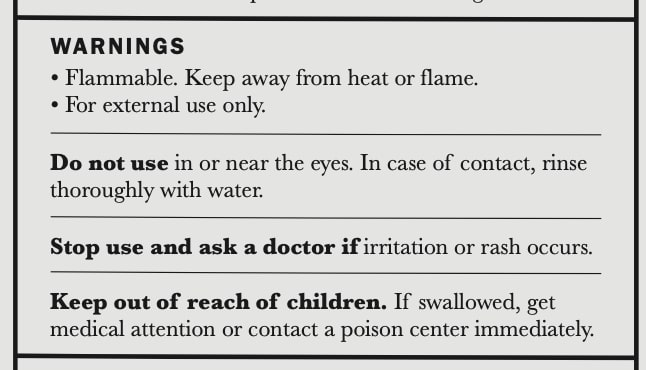 DRUG LABEL: AMASS Four Thieves Sanitizer
NDC: 77419-2000 | Form: LIQUID
Manufacturer: AMASS Brands, Inc
Category: otc | Type: HUMAN OTC DRUG LABEL
Date: 20200711

ACTIVE INGREDIENTS: ALCOHOL 43.66 mL/59 mL
INACTIVE INGREDIENTS: ROSEMARY OIL 0.00390875 mL/59 mL; CINNAMON OIL 0.03127 mL/59 mL; LEMON OIL 0.015635 mL/59 mL; ALLSPICE OIL 0.015635 mL/59 mL; WATER 13.5523 mL/59 mL; GLYCEROL FORMAL 1.475 mL/59 mL; EUCALYPTUS OIL 0.171985 mL/59 mL; CLOVE OIL 0.00390875 mL/59 mL

Active Ingredients ......... Purpose
70% Ethyl Alcohol (v/v)........ Antiseptic

Do not use in or near the eyes. In case of contat, rinse thoroughly with water.

Keep out of reach of children. If swallowed, get medical attention or contact a poison center immediately.

USE
Hand sanitizer to help reduce disease-causing bacteria

Stop use and ask a doctor if irriation or rash occurs.

Directions
Apply liberally to dry hands, rub briskly until evaporated
Children should be supervised when using this product

OTHER INFORMATION
Avoid freezing and excessive heat above 104F (40C)

WARNINGS
Flammable. Keep away from heat or flame.
For external use only.
Do not use in or near the eyes. In case of contact, rinse thoroughly with water.
Stop use and ask a doctor if irritation or rash occurs.
Keep out of reach of children. IF swallowed, get medical attention or contact a poison center immediately.

DIRECTIONS
Apply liberally to dry hands, rub briskly until evaporated.
Children should be supervised when using this product

INACTIVE INGREDIENTS

Aqua, Glycerin, Eucalyptus Obliqua (Eucalyptus) Oil, Salvia Rosmarinus (Rosemary) Oil, Syzygium Aromaticum (Clove) Oil, Cinnamomum Verum (Cinnamon) Oil, Lemon Oil, Pimenta Dioica (Allspice) Oil

DIRECTIONS
Apply liberally to dry hands, rub briskly until evaporated.
Children should be supervised when using this product

WARNINGS
Flammable. Keep away from heat or flame.
For external use only.
Do not use in or near the eyes. In case of contact, rinse thoroughly with water.
Stop use and ask a doctor if irritation or rash occurs.
Keep out of reach of children. IF swallowed, get medical attention or contact a poison center immediately.

USE
Hand sanitizer to help reduce disease-causing bacteria.

PACKAGE LABEL

THE LANBY | AMASS

FOUR THIEVES

CINNAMON

ALLSPICE

CLOVE

EUCALYPTUS

70% Alcohol-based hand sanitizer for when water is unavailable. Manufactured in Los Angeles, California.

16 oz | 473 ml

-----------------Premium Botanics